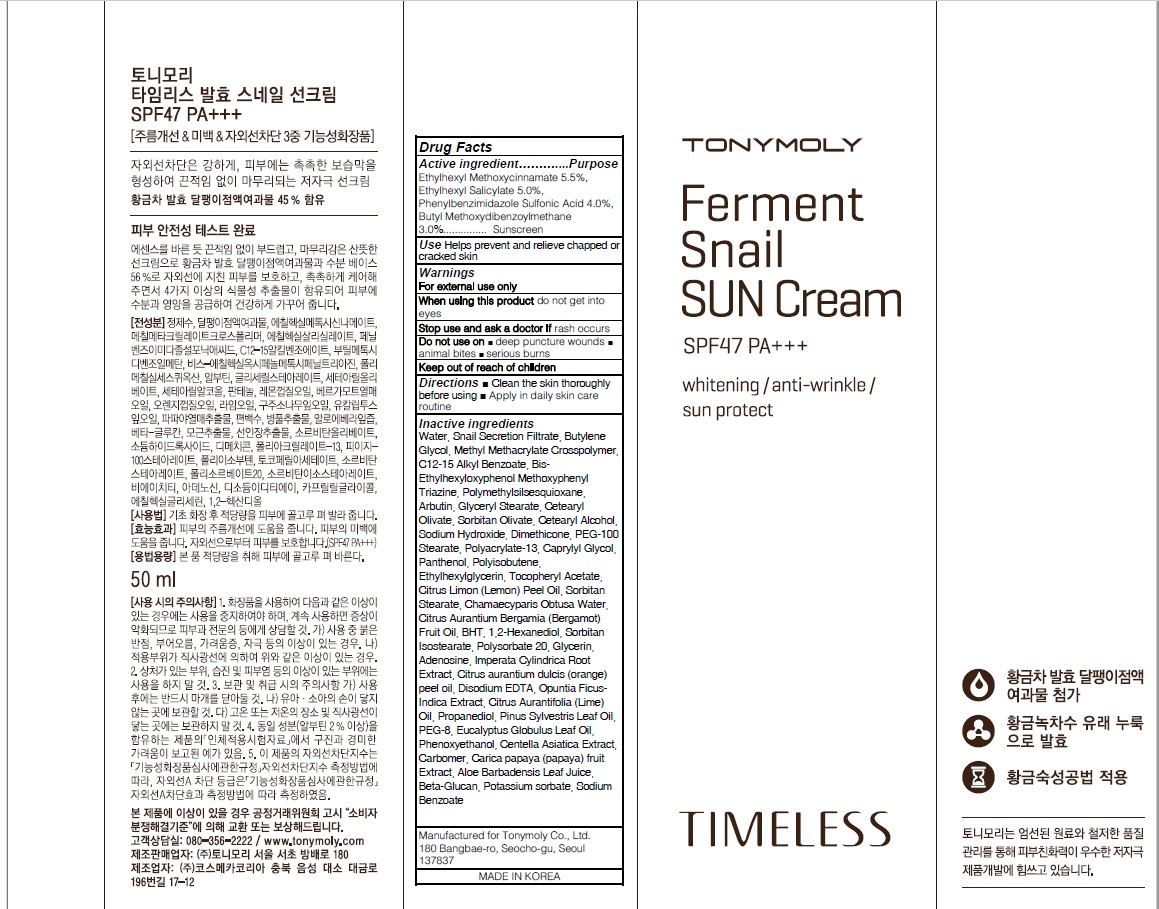 DRUG LABEL: TIMELESS FERMENT SANIL SUN
NDC: 59078-310 | Form: CREAM
Manufacturer: TONYMOLY CO.,LTD
Category: otc | Type: HUMAN OTC DRUG LABEL
Date: 20160614

ACTIVE INGREDIENTS: Octinoxate 2.75 g/50 mL; Octisalate 2.50 g/50 mL; ENSULIZOLE 2.00 g/50 mL; AVOBENZONE 1.50 g/50 mL
INACTIVE INGREDIENTS: Water; Butylene Glycol

ACTIVE INGREDIENT

Active ingredient: Ethylhexyl Methoxycinnamate 5.5%, Ethylhexyl Salicylate 5.0%, Phenylbenzimidazole Sulfonic Acid 4.0%, Butyl Methoxydibenzoylmethane 3.0%

INACTIVE INGREDIENT

Inactive Ingredient: Water, Snail Secretion Filtrate, Butylene Glycol, Methyl Methacrylate Crosspolymer, C12-15 Alkyl Benzoate, Bis-Ethylhexyloxyphenol Methoxyphenyl Triazine, Polymethylsilsesquioxane, Arbutin, Glyceryl Stearate, Cetearyl Olivate, Sorbitan Olivate, Cetearyl Alcohol, Sodium Hydroxide, Dimethicone, PEG-100 Stearate, Polyacrylate-13, Caprylyl Glycol, Panthenol, Polyisobutene, Ethylhexylglycerin, Tocopheryl Acetate, Citrus Limon (Lemon) Peel Oil, Sorbitan Stearate, Chamaecyparis Obtusa Water, Citrus Aurantium Bergamia (Bergamot) Fruit Oil, BHT, 1,2-Hexanediol, Sorbitan Isostearate, Polysorbate 20, Glycerin, Adenosine, Imperata Cylindrica Root Extract, Citrus aurantium dulcis (orange) peel oil, Disodium EDTA, Opuntia Ficus-Indica Extract, Citrus Aurantifolia (Lime) Oil, Propanediol, Pinus Sylvestris Leaf Oil, PEG-8, Eucalyptus Globulus Leaf Oil, Phenoxyethanol, Centella Asiatica Extract, Carbomer, Carica papaya (papaya) fruit Extract, Aloe Barbadensis Leaf Juice, Beta-Glucan, Potassium sorbate, Sodium Benzoate

PURPOSE

Purpose: Sunscreen

WARNINGS

Warnings: For external use only. When using this product do not get into eyes. Stop use and ask a doctor if rash occurs. Do not use on - deep puncture wounds - animal bites - serious burns Keep out of reach of children.

KEEP OUT OF REACH OF CHILDREN

DESCRIPTION

Use: Helps prevent and relieve chapped or cracked skin.

Directions: - Clean the skin thoroughly before using - Apply in daily skin care routine